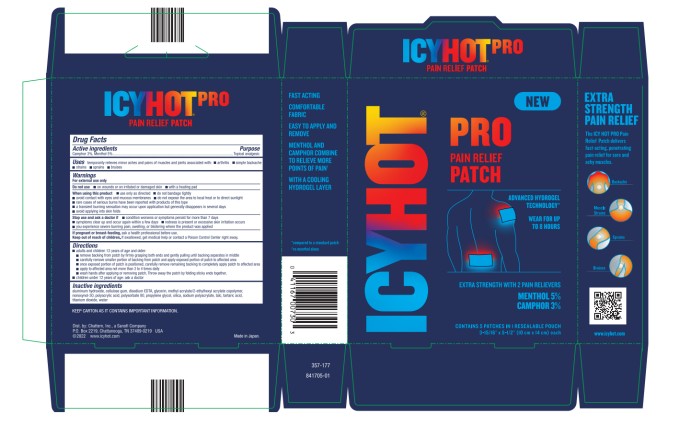 DRUG LABEL: Icy Hot Pro Pain
NDC: 41167-0074 | Form: PATCH
Manufacturer: Chattem, Inc.
Category: otc | Type: HUMAN OTC DRUG LABEL
Date: 20250709

ACTIVE INGREDIENTS: CAMPHOR (SYNTHETIC) 180 mg/1 1; MENTHOL 300 mg/1 1
INACTIVE INGREDIENTS: ALUMINUM HYDROXIDE; CARBOXYMETHYLCELLULOSE SODIUM, UNSPECIFIED; EDETATE DISODIUM ANHYDROUS; GLYCERIN; METHYL ACRYLATE; ETHYLHEXYL ACETATE; NONOXYNOL-30; POLYACRYLIC ACID (250000 MW); PROPYLENE GLYCOL; POLYSORBATE 80; SILICON DIOXIDE; SODIUM POLYACRYLATE (2500000 MW); TALC; TARTARIC ACID; TITANIUM DIOXIDE; WATER

Icy Hot Pro Pain Patch

ICY HOT PRO PAIN PATCH

Drug Facts

Active ingredients

Camphor 3%

Menthol 5%

Purpose

Topical analgesic

Topical analgesic

Uses

temporarily relieves minor aches and pains of muscles and joints associated with: ■ arthritis ■ simple backache ■ strains ■ sprains ■ bruises

Warnings

For external use only

Do not use

■ on wounds or on irritated or damaged skin

■ with a heating pad

When using this product

■ use only as directed

■ do not bandage tightly

■ avoid contact with eyes and mucous membranes

■ do not expose the area to local heat or to direct sunlight

■ rare cases of serious burns have been reported with products of this type

■ a transient burning sensation may occur upon application but generally disappears in several days

■ avoid applying into skin folds

Stop use and ask a doctor if

■ condition worsens or symptoms persist for more than 7 days

■ symptoms clear up and occur again within a few days

■ redness is present or excessive skin irritation occurs

■ you experience severe burning pain, swelling, or blistering where the product was applied

If pregnant or breast-feeding,

ask a health professional before use.

Keep out of reach of children.

If swallowed, get medical help or contact a Poison Control Center right away.

Directions

■ adults and children 12 years of age and older:

■ remove backing from patch by firmly grasping both ends and gently pulling until backing separates in middle

■ carefully remove smaller portion of backing from patch and apply exposed portion of patch to affected area

■ once exposed portion of patch is positioned, carefully remove remaining backing to completely apply patch to affected area

■ apply to affected area not more than 3 to 4 times daily

■ wash hands after applying or removing patch. Throw away the patch by folding sticky ends together.

■ children under 12 years of age: ask a doctor

Inactive ingredients

aluminum hydroxide, cellulose gum, disodium EDTA, glycerin, methyl acrylate/2-ethylhexyl acrylate copolymer, nonoxynol-30, polyacrylic acid, polysorbate 80, propylene glycol, silica, sodium polyacrylate, talc, tartaric acid, titanium dioxide, water

Keep carton as it contains important information.

Principal Display Panel

ICY HOT PRO
PAIN RELIEF PATCH
EXTRA STRENGTH WITH 2 PAIN RELIEVERS
MENTHOL 5%
CAMPHOR 3%
CONTAINS 5 PATCHES IN 1 RESEALABLE POUCH